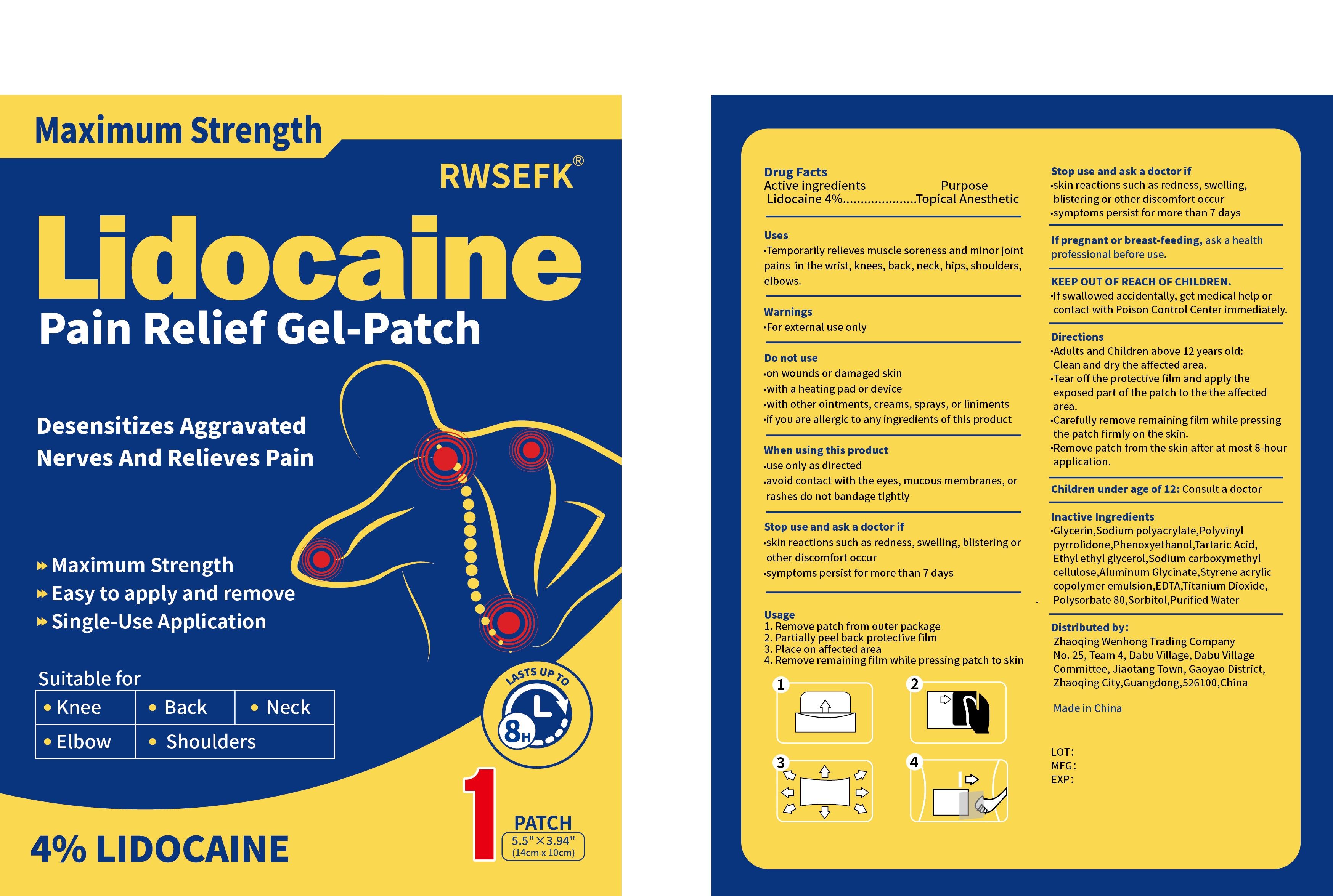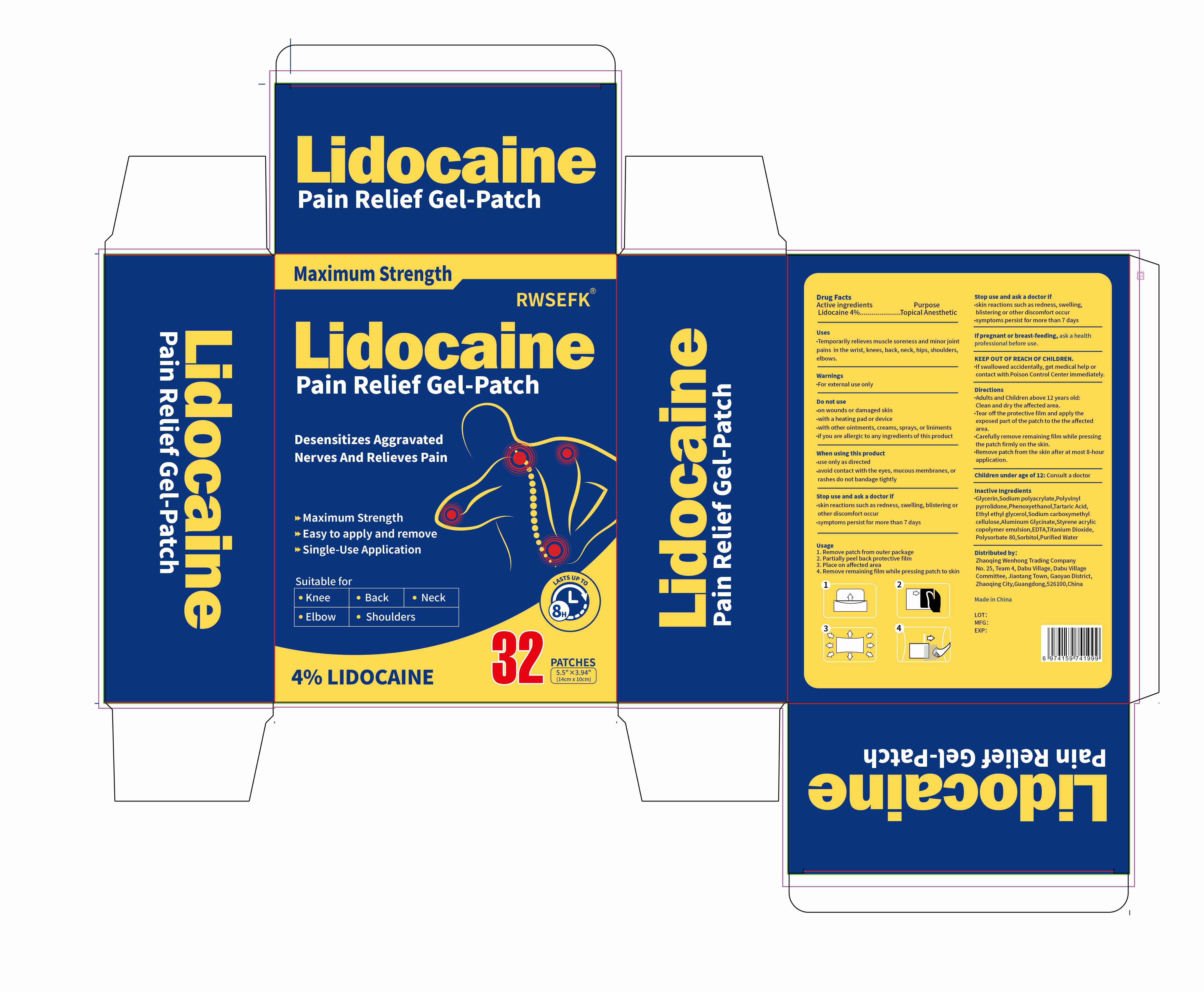 DRUG LABEL: RWSEFK Lidocaine Pain Relief Gel-Patch
NDC: 83559-008 | Form: PATCH
Manufacturer: Henan Enokon Medical Instrument Co., Ltd.
Category: otc | Type: HUMAN OTC DRUG LABEL
Date: 20250325

ACTIVE INGREDIENTS: LIDOCAINE 4 g/100 1
INACTIVE INGREDIENTS: ETHYLHEXYLGLYCERIN; TARTARIC ACID; GLYCERIN; CARBOXYMETHYLCELLULOSE SODIUM; TITANIUM DIOXIDE; POLYSORBATE 80; SODIUM ACRYLATE; WATER; STYRENE/ACRYLAMIDE COPOLYMER (500000 MW); POVIDONE; SORBITOL; EDTA; PHENOXYETHANOL; ALUMINUM GLYCINATE

83559-008

Active Ingredient

Lidocaine 4%

Purpose

Topical anesthetic

Use

Temporarily relieves muscle soreness and minor joint pains in the wrist, knees, back, neck, hips, shoulders, elbows.

Warnings

For external use only

Do not use

on wounds or damaged skin
with a heating pad or device
with other ointments, creams, sprays, or liniments
if you are allergic to any ingredients of this product

When Using

When using this product
use only as directed
avoid contact with the eyes, mucous membranes or rashes
do not bandage tightly

Stop Use

Stop use and ask a doctor if
on wounds or damaged skin
with a heating pad or device
with other ointments, creams, sprays, or liniments
if you are allergic to any ingredients of this product

Ask Doctor

If pregnant or breast-feeding, ask a health professional before use.
Children under age of 12: Consult a doctor

Keep Out Of Reach Of Children

If swallowed accidentally, get medical help or contact with Poison Control Center immediately.

Directions

Adults and Children above 12 years old:
Clean and dry the affected area.
Tear off the protective film and apply the exposed part of the patch to the the affected area.
Carefully remove remaining film while pressing the patch firmly on the skin.
Remove patch from the skin after at most 8-hour application.

Inactive ingredients

Glycerin,Sodium polyacrylate,Polyvinyl pyrrolidone,Phenoxyethanol,Tartaric Acid,Ethyl ethyl glycerol,Sodium carboxymethyl cellulose,Aluminum Glycinate,Styrene acrylic copolymer emulsion,EDTA,Titanium Dioxide,Polysorbate 80,Sorbitol,Purified Water